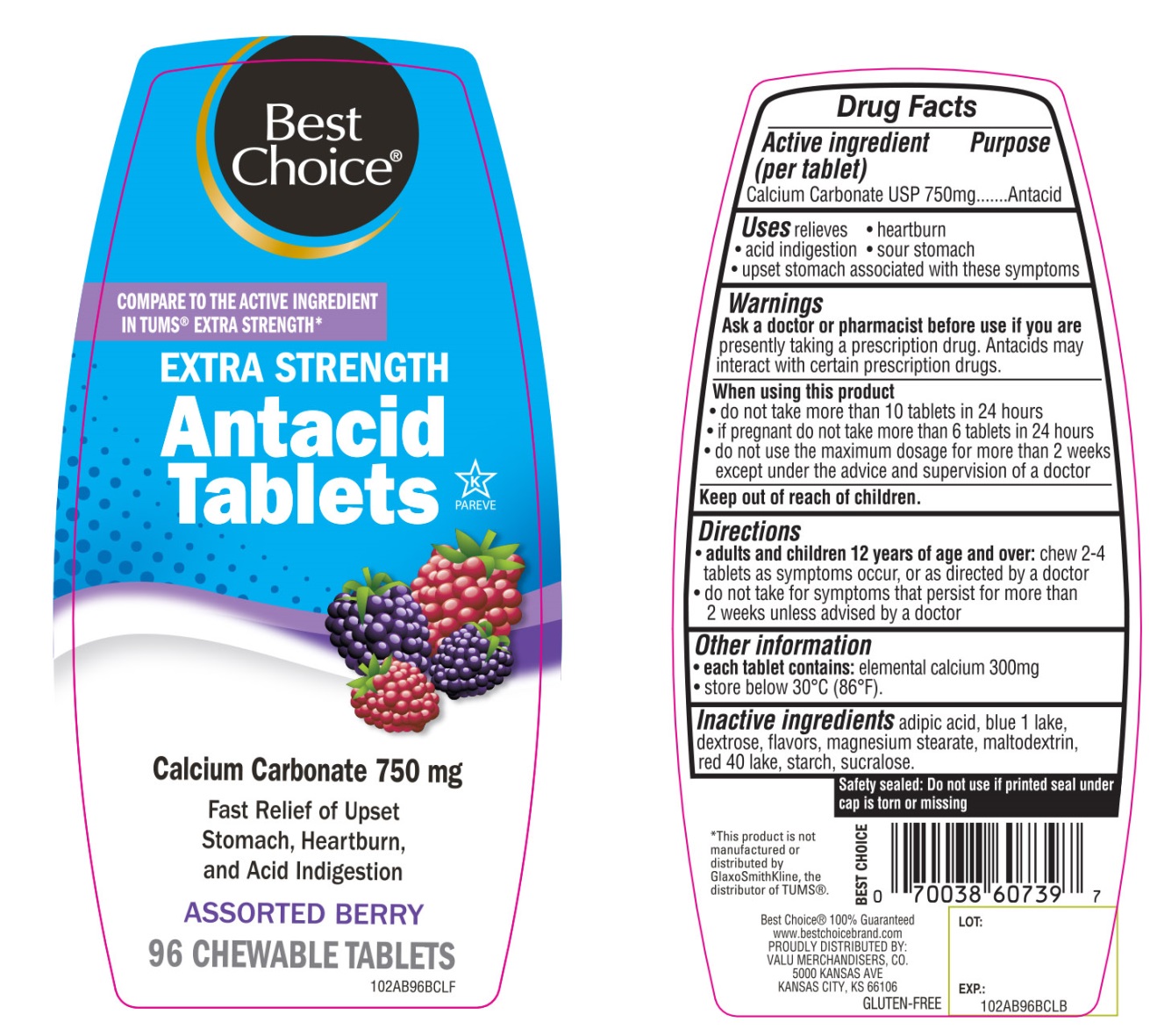 DRUG LABEL: Best Choice Extra Strength

NDC: 63941-021 | Form: TABLET, CHEWABLE
Manufacturer: BEST CHOICE (VALU MERCHANDISERS COMPANY)
Category: otc | Type: HUMAN OTC DRUG LABEL
Date: 20250715

ACTIVE INGREDIENTS: CALCIUM CARBONATE 750 mg/1 1
INACTIVE INGREDIENTS: ADIPIC ACID; FD&C BLUE NO. 1; DEXTROSE, UNSPECIFIED FORM; MAGNESIUM STEARATE; MALTODEXTRIN; FD&C RED NO. 40; STARCH, CORN; SUCRALOSE

Extra Strength Calcium Carbonate Assorted Berries 96 Chewable Tablets

Active ingredient (per tablet)

Calcium Carbonate USP 750mg

Purpose

Antacid

Uses

relieves

- heartburn
- acid indigestion
- sour stomach
- upset stomach associated with these symptoms

Warnings

Ask a doctor or pharmacist before use if you arepresently taking a prescription drug. Antacids may interact with certain prescription drugs.

When using this product

- do not take more than 10 tablets in 24 hours
- If pregnant do not take more than 6 tablets in 24 hours
- do not use the maximum dosage for more than 2 weeks except under the advice and supervision of a doctor

Directions

- adults and children 12 years of age and over:chew 2-4 tablets as symptoms occur or as directed by a doctor.
- do not take for symptoms that persist for more than 2 weeks unless advised by a doctor.

Other Information

- each tablet contains:elemental calcium 300mg
- store below 30°C (86°F)

SAFETY SEALED: DO NOT USE IF PRINTED SEAL UNDER CAP IS TORN OR MISSING

Inactive ingredients

adipic acid, blue 1 lake, dextrose, flavors, magnesium stearate, maltodextrin, red 40 lake, starch, sucralose.

Package/Label Principal Display Panel

Best Choice®

NDC# 63941-021-96

COMPARE TO THE ACTIVE INGREDIENT IN TUMS®EXTRA STRENGTH*

EXTRA STRENGTH

Antacid Tablets

Calcium Carbonate 750 mg

Fast Relief of Upset Stomach, Heartburn and Acid Indigestion

ASSORTED BERRY

96 CHEWABLE TABLETS

K PAREVE

GLUTEN-FREE

Best Choice® 100% Guaranteed www.bestchoicebrand.com

PROUDLY DISTRIBUTED BY:

VALU MERCHANDISERS, CO.

5000 KANSAS AVE

KANSAS CITY, KS 66106

*This product is not manufactured or distributed by GlaxoSmithKline, the distributor of TUMS®.